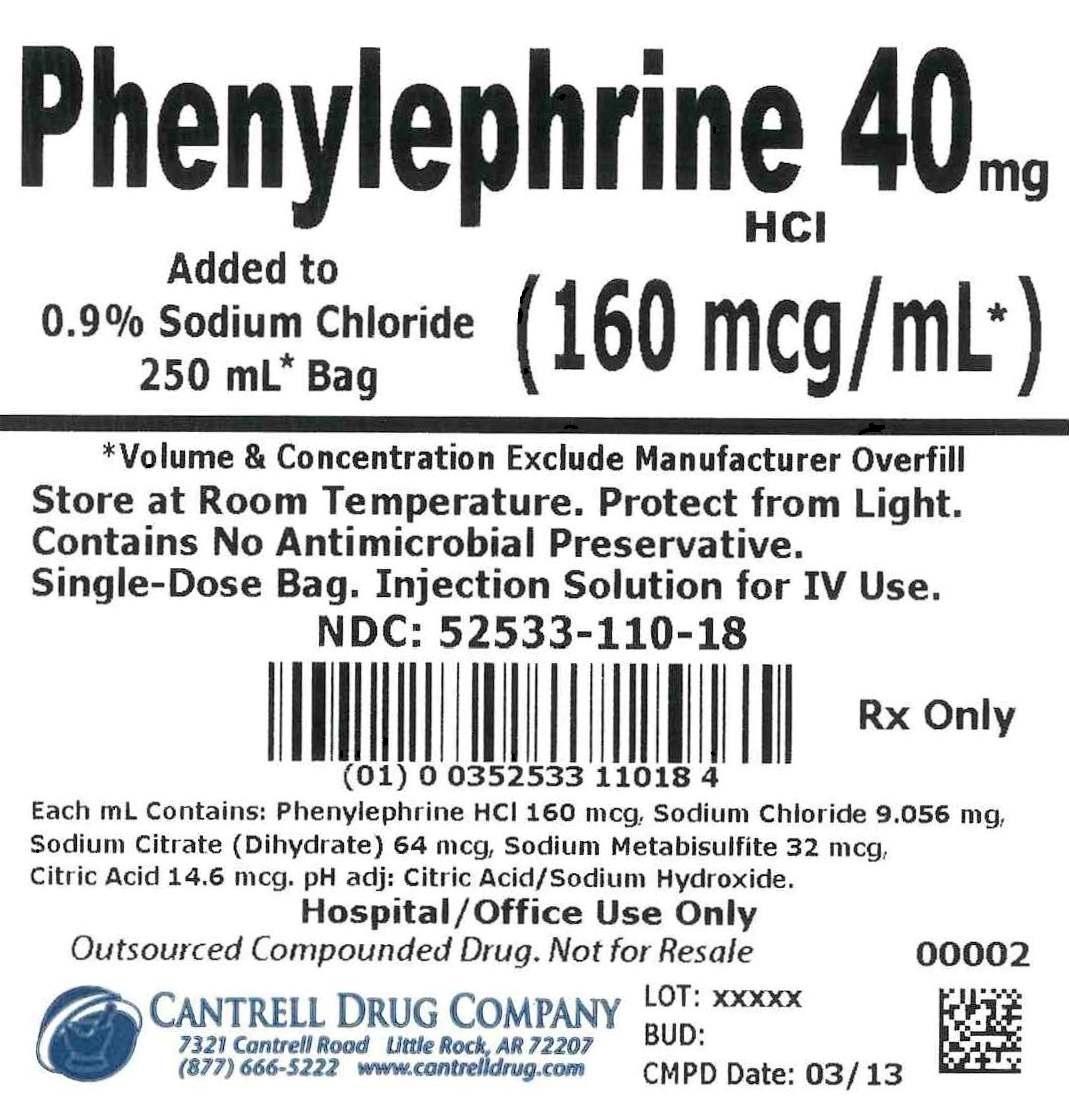 DRUG LABEL: Phenylephrine HCl
NDC: 52533-110 | Form: INJECTION, SOLUTION
Manufacturer: Cantrell Drug Company
Category: prescription | Type: HUMAN PRESCRIPTION DRUG LABEL
Date: 20150814

ACTIVE INGREDIENTS: Phenylephrine Hydrochloride 160 ug/1 mL
INACTIVE INGREDIENTS: Sodium Chloride 9.056 mg/1 mL; TRISODIUM CITRATE DIHYDRATE 64 ug/1 mL; SODIUM METABISULFITE 32 ug/1 mL; CITRIC ACID MONOHYDRATE 14.6 ug/1 mL; WATER

Phenylephrine HCl 40 mg Added to 0.9% Sodium Chloride 250 mL Bag